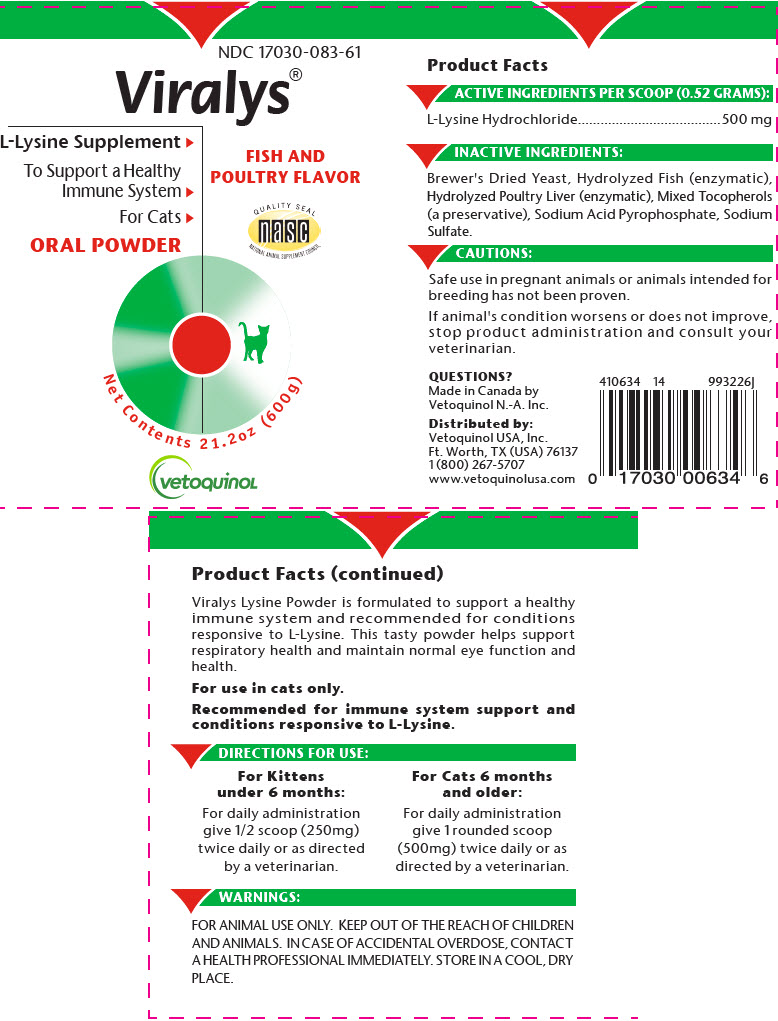 DRUG LABEL: VIRALYS
NDC: 17030-083 | Form: POWDER
Manufacturer: Vetoquinol USA, Inc.
Category: animal | Type: OTC ANIMAL DRUG LABEL
Date: 20200213

ACTIVE INGREDIENTS: LYSINE HYDROCHLORIDE 500 mg/0.52 g
INACTIVE INGREDIENTS: SACCHAROMYCES CEREVISIAE; TOCOPHEROL; SODIUM ACID PYROPHOSPHATE; SODIUM SULFATE

VIRALYS®

Product Facts

DESCRIPTION

ACTIVE INGREDIENTS PER SCOOP (0.52 GRAMS):

L-Lysine Hydrochloride | 500 mg

INACTIVE INGREDIENTS:

Brewer's Dried Yeast, Hydrolyzed Fish (enzymatic), Hydrolyzed Poultry Liver (enzymatic), Mixed Tocopherols (a preservative), Sodium Acid Pyrophosphate, Sodium Sulfate.

PRECAUTIONS

CAUTIONS:

Safe use in pregnant animals or animals intended for breeding has not been proven.

If animal's condition worsens or does not improve, stop product administration and consult your veterinarian.

VETERINARY INDICATIONS

Viralys Lysine Powder is formulated to support a healthy immune system and recommended for conditions responsive to L-Lysine. This tasty powder helps support respiratory health and maintain normal eye function and health.

For use in cats only.

Recommended for immune system support and conditions responsive to L-Lysine.

DOSAGE AND ADMINISTRATION

DIRECTIONS FOR USE:

For Kittens under 6 months: | For Cats 6 months and older:
For daily administration give 1/2 scoop (250mg) twice daily or as directed by a veterinarian. | For daily administration give 1 rounded scoop (500mg) twice daily or as directed by a veterinarian.

WARNINGS:

FOR ANIMAL USE ONLY. KEEP OUT OF THE REACH OF CHILDREN AND ANIMALS. IN CASE OF ACCIDENTAL OVERDOSE, CONTACT A HEALTH PROFESSIONAL IMMEDIATELY. STORE IN A COOL, DRY PLACE.

QUESTIONS?
Made in Canada by
Vetoquinol N.-A. Inc.

Distributed by:
Vetoquinol USA, Inc.
Ft. Worth, TX (USA) 76137
1 (800) 267-5707
www.vetoquinolusa.com

410634 14 993226J

PRINCIPAL DISPLAY PANEL - 600 g Container Label

NDC 17030-083-61

Viralys®

L-Lysine Supplement ⯈

To Support a Healthy
Immune System ⯈

For Cats ⯈

ORAL POWDER

FISH AND
POULTRY FLAVOR

QUALITY SEAL
nasc
NATIONAL ANIMAL SUPPLEMENT COUNCIL

Net Contents 21.2oz (600g)

vetoquinol